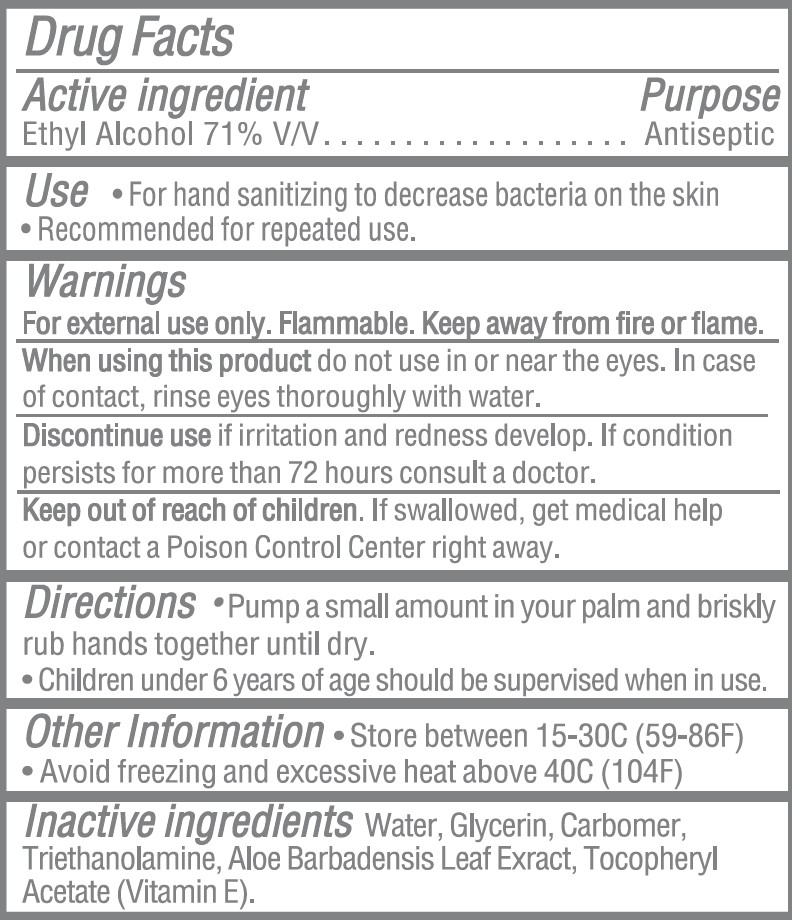 DRUG LABEL: Moxie Hand Sanitizing Gel
NDC: 77720-033 | Form: GEL
Manufacturer: Skaffles Group
Category: otc | Type: HUMAN OTC DRUG LABEL
Date: 20250302

ACTIVE INGREDIENTS: ALCOHOL 71 mL/100 mL
INACTIVE INGREDIENTS: WATER; GLYCERIN; CARBOMER INTERPOLYMER TYPE A (ALLYL SUCROSE CROSSLINKED); TROLAMINE; ALOE VERA LEAF; ALPHA-TOCOPHEROL ACETATE

Moxie Hand Sanitizer Gel

Drug Facts

Active Ingredient

Ethyl Alcohol 71% V/V

Purpose

Antiseptic

Use

- for hand sanitizing to decrease bacteria on the skin
- recommended for repeated use

Warnings

For external use only. Flammable. Keep away from fire or flame.

WHEN USING

When using this productdo not use in or near the eyes. In case of contact, rinse eyes thoroughly with water

STOP USE

Discontinue Use if irritation and redness develop. If condition persists for more than 72 hours consult a doctor

Keep out of reach of children. If swallowed, get medical help or contact a Poison Control Center right away.

Directions

- Pump a small amount in your palm and briskly rub hands together until dry.
- Children under 6 years of age should be supervised when in use.

Other Information

Store between 15-30C (59-89F)

Avoid freezing and excessive heat above 40C (104F)

Inactive ingredients

Water, Glycerin, Carbomer, Triethanolamine, Aloe Barbadensis Leaf Juice, Tocopheryl Acetate (Vitamin E).

QUESTIONS

Ditributed by: Lowe's Home Centers LLC

Mooresville NC 28117

Principal Display Panel

Moxie

HAND SANITIZER GEL

Kills 99.9% of most common germs

Moisturizes with Aloe & Vitamin E

Light & Fresh Scent

16.9 FL OZ (500ml)

MADE IN CHINA

Item

Model

MOXIE and logo deisign are trademarks or registered trademarks of LF, LLC. All rights reserved.